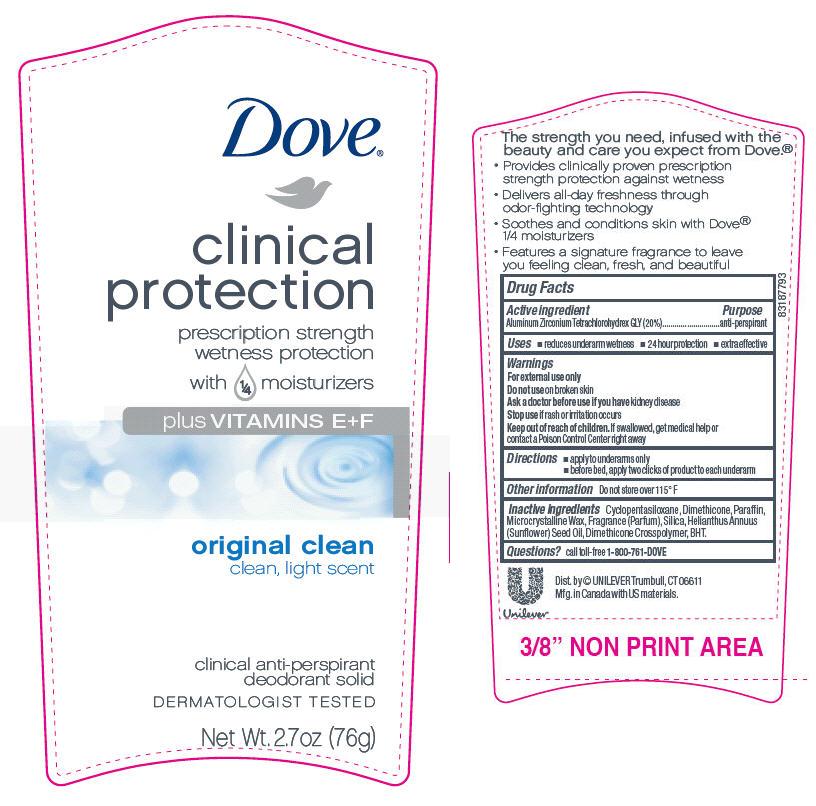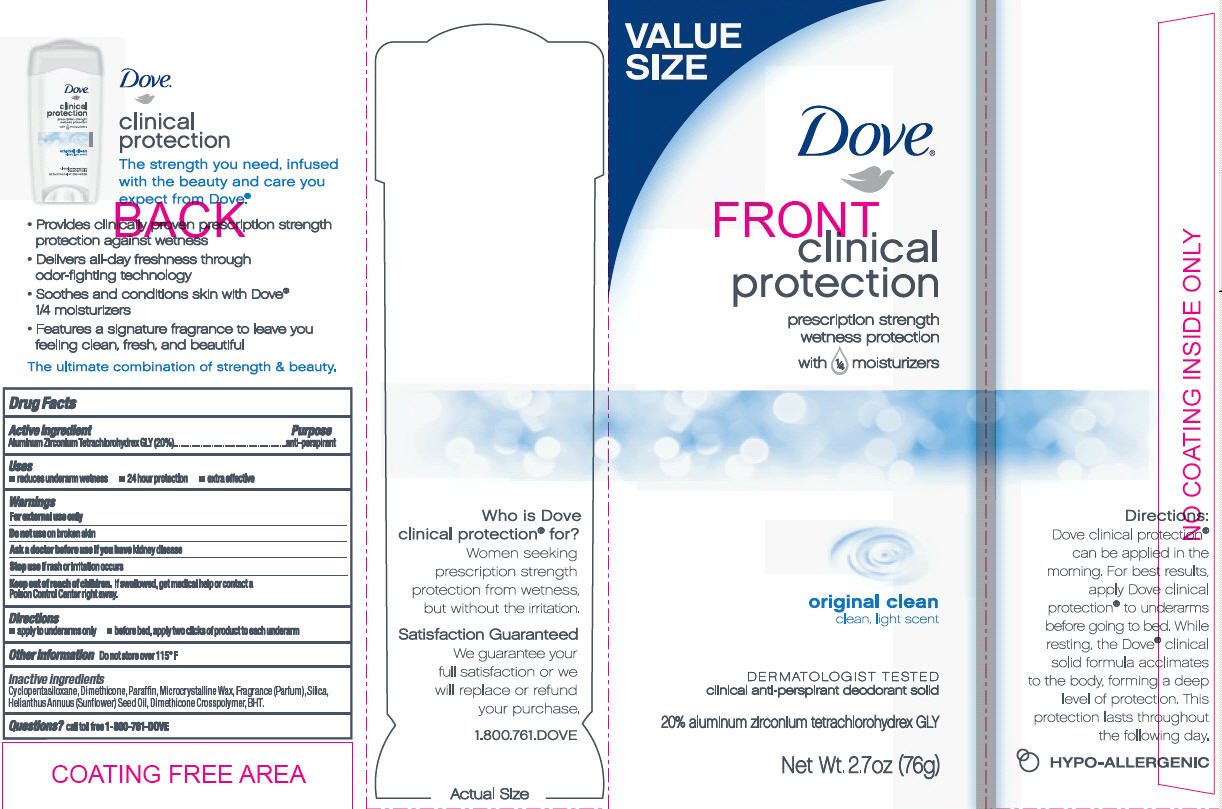 DRUG LABEL: Dove Clinical Protection Original Clean
NDC: 64942-1010 | Form: STICK
Manufacturer: Conopco Inc. d/b/a Unilever
Category: otc | Type: HUMAN OTC DRUG LABEL
Date: 20120131

ACTIVE INGREDIENTS: Aluminum Zirconium Tetrachlorohydrex GLY 20 g/100 g
INACTIVE INGREDIENTS: CYCLOMETHICONE 5; DIMETHICONE; BUTYLATED HYDROXYTOLUENE; PARAFFIN; MICROCRYSTALLINE WAX; SILICON DIOXIDE; SUNFLOWER OIL

Dove Clinical Protection Original Clean antiperspirant deodorant

Active Ingredient

Aluminum Zirconium Tetrachlorohydrex GLY (20%)

Purpose
anti-perspirant

Uses
· reduces underarm wetness
· 24 hour protection
· extra effective

Warnings
For external use only

Do not use on broken skin

Ask a doctor before use if you have kidney disease

Stop use if rash or irritation occurs

Keep out of reach of children. If swallowed, get medical help or contact a Poison Control Center right away.

Directions
· apply to underarms only
· before bed, apply three clicks of product to each underarm

INACTIVE INGREDIENT

Cyclopentasiloxane, Dimethicone, Paraffin, Microcrystalline Wax, Fragrance (Parfum), Silica, Helianthus Annuus (Sunflower) Seed Oil, Dimethicone Crosspolymer, BHT.

Questions? Call toll-free 1-800-761-DOVE

PACKAGE LABEL

PDP 2.7 oz.

PACKAGE LABEL

2.7 oz Carton